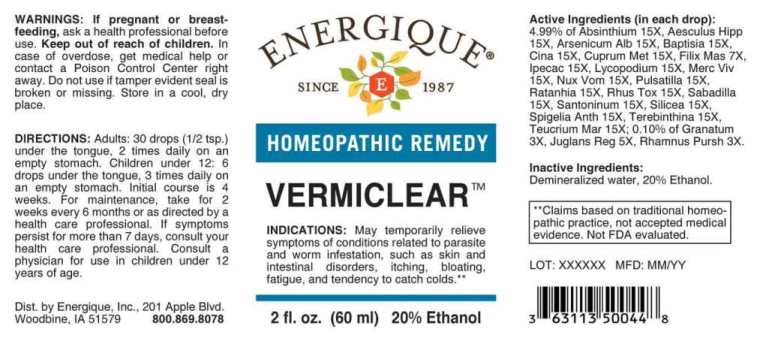 DRUG LABEL: Vermiclear
NDC: 44911-0610 | Form: LIQUID
Manufacturer: Energique, Inc.
Category: homeopathic | Type: HUMAN OTC DRUG LABEL
Date: 20240813

ACTIVE INGREDIENTS: PUNICA GRANATUM ROOT BARK 3 [hp_X]/1 mL; FRANGULA PURSHIANA BARK 3 [hp_X]/1 mL; JUGLANS REGIA LEAF 5 [hp_X]/1 mL; DRYOPTERIS FILIX-MAS ROOT 7 [hp_X]/1 mL; WORMWOOD 15 [hp_X]/1 mL; HORSE CHESTNUT 15 [hp_X]/1 mL; ARSENIC TRIOXIDE 15 [hp_X]/1 mL; BAPTISIA TINCTORIA WHOLE 15 [hp_X]/1 mL; ARTEMISIA CINA PRE-FLOWERING TOP 15 [hp_X]/1 mL; COPPER 15 [hp_X]/1 mL; IPECAC 15 [hp_X]/1 mL; LYCOPODIUM CLAVATUM SPORE 15 [hp_X]/1 mL; MERCURY 15 [hp_X]/1 mL; STRYCHNOS NUX-VOMICA SEED 15 [hp_X]/1 mL; PULSATILLA VULGARIS 15 [hp_X]/1 mL; KRAMERIA LAPPACEA ROOT 15 [hp_X]/1 mL; TOXICODENDRON PUBESCENS LEAF 15 [hp_X]/1 mL; SCHOENOCAULON OFFICINALE SEED 15 [hp_X]/1 mL; SANTONIN 15 [hp_X]/1 mL; SILICON DIOXIDE 15 [hp_X]/1 mL; SPIGELIA ANTHELMIA WHOLE 15 [hp_X]/1 mL; TURPENTINE OIL 15 [hp_X]/1 mL; TEUCRIUM MARUM WHOLE 15 [hp_X]/1 mL
INACTIVE INGREDIENTS: WATER; ALCOHOL

DRUG FACTS:

ACTIVE INGREDIENTS:

(in each drop): 4.99% of Absinthium 15X, Aesculus Hippocastanum 15X, Arsenicum Album 15X, Baptisia Tinctoria 15X, Cina 15X, Cuprum Metallicum 15X, Filix Mas 7X, Ipecacuanha 15X, Lycopodium Clavatum 15X, Mercurius Vivus 15X, Nux Vomica 15X, Pulsatilla (Vulgaris) 15X, Ratanhia 15X, Rhus Tox 15X, Sabadilla 15X, Santoninum 15X, Silicea 15X, Spigelia Anthelmia 15X,Terebinthina 15X, Teucrium Marum 15X; 0.10% of Granatum 3X, Juglans Regia 5X, Rhamnus Purshiana 3X.

INDICATIONS:

May temporarily relieve symptoms of conditions related to parasite and worm infestation, such as skin and intestinal disorders, itching, bloating, fatigue, and tendency to catch colds.**

**Claims based on traditional homeopathic practice, not accepted medical evidence. Not FDA evaluated.

WARNINGS:

If pregnant or breast-feeding, ask a health professional before use.

Keep out of reach of children. In case of overdose get medical help or contact a Poison Control Center right away.

Do not use if tamper evident seal is broken or missing. Store in a cool, dry place.

Keep out of reach of children. In case of overdose get medical help or contact a Poison Control Center right away.

DIRECTIONS:

Adults: 30 drops (1/2 tsp.) under the tongue, 2 times daily on an empty stomach. Children under 12: 6 drops under the tongue, 3 times daily on an empty stomach. Initial course is 4 weeks. For maintenance, take for 2 weeks every 6 months or as directed by a health care professional. If symptoms persist for more than 7 days, contact your health care professional. Consult a physician for use in children under 12 years of age.

INDICATIONS:

May temporarily relieve symptoms of conditions related to parasite and worm infestation, such as skin and intestinal disorders, itching, bloating, fatigue, and tendency to catch colds.**

**Claims based on traditional homeopathic practice, not accepted medical evidence. Not FDA evaluated.

INACTIVE INGREDIENTS:

Demineralized water, 20% Ethanol.

QUESTIONS:

Dist. by Energique, Inc.

201 Apple Blvd.

Woodbine, IA 51579 800.869.8078

PACKAGE LABEL DISPLAY:

ENERGIQUE

SINCE 1987

HOMEOPATHIC REMEDY

VERMICLEAR

2 fl. oz. (60 ml)